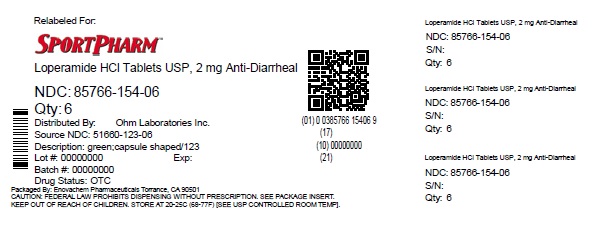 DRUG LABEL: Loperamide Hydrochloride
NDC: 85766-154 | Form: TABLET
Manufacturer: Sportpharm LLC
Category: otc | Type: HUMAN OTC DRUG LABEL
Date: 20260206

ACTIVE INGREDIENTS: LOPERAMIDE HYDROCHLORIDE 2 mg/1 1
INACTIVE INGREDIENTS: ANHYDROUS LACTOSE; CROSCARMELLOSE SODIUM; CROSPOVIDONE (15 MPA.S AT 5%); D&C YELLOW NO. 10; FD&C BLUE NO. 1; HYDROGENATED COTTONSEED OIL; MAGNESIUM STEARATE; POWDERED CELLULOSE; STARCH, CORN

Loperamide Hydrochloride Tablets USP, 2 mg

Drug Facts

Active ingredient (in each caplet)

Loperamide Hydrochloride USP, 2 mg

Purpose

Anti-diarrheal

Use

controls symptoms of diarrhea, including Travelers' Diarrhea

Warnings

Allergy alert:Do not use if you have ever had a rash or other allergic reaction to loperamide hydrochloride

Heart alert:Taking more than directed can cause serious heart problems or death

DO NOT USE

Do not useif you have bloody or black stool

Ask a doctor before use if you have

- fever
- mucus in the stool
- a history of liver disease
- a history of abnormal heart rhythm

Ask a doctor or pharmacist before use if you aretaking a prescription drug. Loperamide may interact with certain prescription drugs.

WHEN USING

When using this producttiredness, drowsiness or dizziness may occur. Be careful when driving or operating machinery.

Stop use and ask a doctor if

- symptoms get worse
- diarrhea lasts for more than 2 days
- you get abdominal swelling or bulging. These may be signs of a serious condition.

PREGNANCY OR BREAST FEEDING

If pregnant or breast-feeding,ask a health professional before use.

Keep out of reach of children.In case of overdose, get medical help or contact a Poison Control Center right away (1-800-222-1222).

Directions

- drink plenty of clear fluids to help prevent dehydration caused by diarrhea
- find right dose on chart. If possible, use weight to dose; otherwise, use age.

adults and children; 12 years and over | 2 caplets after the first loose stool; 1 caplet after each subsequent loose stool; but no more than 4 caplets in 24 hours
children 9-11 years; (60-95 lbs) | 1 caplet after the first loose stool; ½ caplet after each subsequent loose stool; but no more than 3 caplets in 24 hours
children 6-8 years; (48-59 lbs) | 1 caplet after the first loose stool; ½ caplet after each subsequent loose stool; but no more than 2 caplets in 24 hours
children 2-5 years; (34 to 47 lbs) | ask a doctor
children under 2 years; (up to 33 lbs) | do not use

Other information

- store between 20° – 25°C (68° – 77°F)
- see side panel for lot number and expiration date
- TAMPER EVIDENT: THIS PRODUCT IS PROTECTED WITH SEALED BLISTER UNITS. DO NOT USE IF ANY ARE TORN OR BROKEN.

Inactive ingredients

anhydrous lactose, croscarmellose sodium, crospovidone, D&C yellow no. 10 aluminum lake, FD&C blue no. 1 aluminum lake, hydrogenated vegetable oil, magnesium stearate, powdered cellulose, pregelatinized starch

Questions?

call 1-800-406-7984

Keep the carton. It contains important information.

Distributed by:

Sportpharm LLC

379 Van Ness Ave 1401,

Torrance, CA 90501

Relabeled by:

Enovachem PHARMACEUTICALS

Torrance, CA 90501